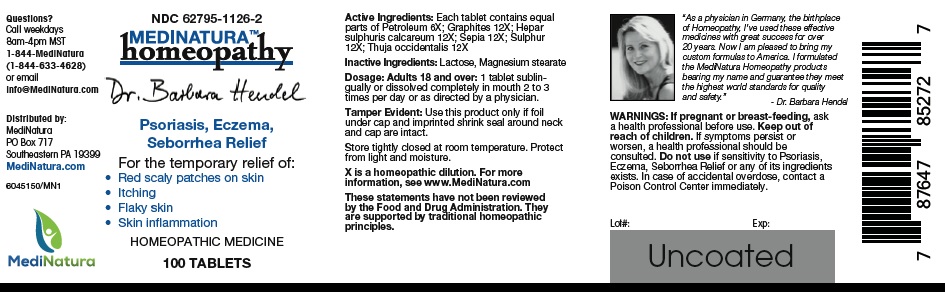 DRUG LABEL: Hendel Psoriasis, Eczema, Seborrhea
NDC: 62795-1126 | Form: TABLET
Manufacturer: MediNatura Inc
Category: homeopathic | Type: HUMAN OTC DRUG LABEL
Date: 20220822

ACTIVE INGREDIENTS: KEROSENE 6 [hp_X]/1 1; GRAPHITE 12 [hp_X]/1 1; CALCIUM SULFIDE 12 [hp_X]/1 1; SEPIA OFFICINALIS JUICE 12 [hp_X]/1 1; SULFUR 12 [hp_X]/1 1; THUJA OCCIDENTALIS LEAFY TWIG 12 [hp_X]/1 1
INACTIVE INGREDIENTS: LACTOSE MONOHYDRATE; MAGNESIUM STEARATE

Hendel Psoriasis, Eczema, Seborrhea

WARNINGS

If pregnant or breast-feeding, ask a health professional before use. Keep out of reach of children. If symptoms persist or worsen, a health professional should be consulted. Do not use if sensitivity to Psoriasis, Eczema, Seborrhea Relief or any of its ingredients exists. In case of accidental overdose, contact a Poison Control Center immediately.

USES

• Red scaly patches on skin
• Itchy
• Flaky skin
• Skin inflammation

KEEP OUT OF REACH OF CHILDREN

DIRECTIONS

Adults 18 and over: 1 tablet sublingually or dissolved completely in mouth 2 to 3 times per day or as directed by a physician

INDICATIONS

Psoriasis, Eczema, Seborrhea Relief

INACTIVE INGREDIENT

Lactose, Magnesium stearate

INGREDIENTS

Each tablet contains equal parts of Petroleum 6X; Graphites 12X; Hepar sulphuris calcareum 12X; Sepia 12X; Sulphur 12X; Thuja occidentalis 12X.

PACKAGE LABEL

Add image transcription here...